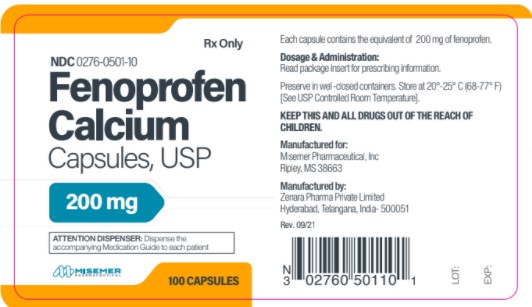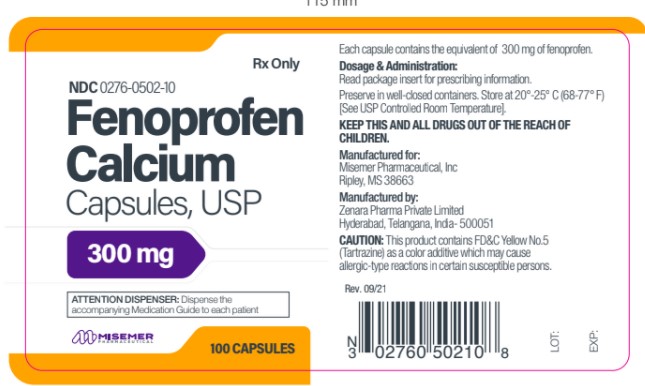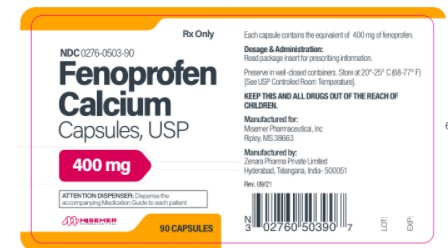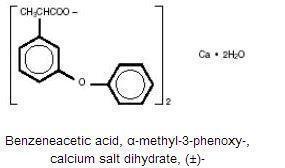 DRUG LABEL: Fenoprofen Calcium
NDC: 0276-0503 | Form: CAPSULE
Manufacturer: Misemer Pharmaceuticals, Inc.
Category: prescription | Type: HUMAN PRESCRIPTION DRUG LABEL
Date: 20250127

ACTIVE INGREDIENTS: FENOPROFEN CALCIUM 400 mg/1 1
INACTIVE INGREDIENTS: CROSPOVIDONE; MAGNESIUM STEARATE; SODIUM LAURYL SULFATE; TALC; GELATIN; TITANIUM DIOXIDE; BROWN IRON OXIDE

HIGHLIGHTS OF PRESCRIBING INFORMATION

These highlights do not include all the information needed to use Fenoprofen Calcium safely and effectively. See full prescribing information for Fenoprofen Calcium. Fenoprofen Calcium, capsules, for oral use
Initial U.S. Approval: 1982

WARNING: RISK OF SERIOUS CARDIOVASCULAR AND GASTROINTESTINAL EVENTS

See full prescribing information for complete boxed warning

- Non-Steroidal Anti-Inflammatory drugs (NSAIDs) cause an increased risk of serious cardiovascular thrombotic events, including myocardial infarction and stroke, which can be fatal. This risk may occur early in treatment and may increase with duration of use. (5.1)

- FENOPROFEN CALCIUM is contraindicated in the setting of coronary artery bypass graft (CABG) surgery (4, 5.1)

- NSAIDs cause an increased risk of serious gastrointestinal (GI) adverse events including bleeding, ulceration, and perforation of stomach or intestines, which can be fatal. These events can occur at any time during use and without warning symptoms. Elderly patients and patients with a prior history of peptic ulcer disease and/or GI bleeding are at greater risk for serious GI events (5.2)

RECENT MAJOR CHANGES

Boxed Warning |  | 4/2016
Warnings and Precautions, Cardiovascular Thrombotic Events (5.1) |  | 4/2016
Warnings and Precautions, Heart Failure and Edema (5.5) |  | 4/2016

1. INDICATIONS AND USAGE

FENOPROFEN CALCIUM is a nonsteroidal anti-inflammatory drug indicated for:

- Relief of mild to moderate pain in adults. (1)
- Relief of the signs and symptoms of rheumatoid arthritis. (1)
- Relief of the signs and symptoms of osteoarthritis. (1)

2. DOSAGE AND ADMINISTRATION

- Use the lowest effective dosage for shortest duration consistent with individual patient treatment goals (2.1)
- Analgesia: For the treatment of mild to moderate pain, the recommended dosage is 200 mg given orally every 4 to 6 hours, as needed (2.1)
- Rheumatoid Arthritis and Osteoarthritis: For the relief of signs and symptoms of rheumatoid arthritis or osteoarthritis the recommended dose is 400 to 600 mg given orally, 3 or 4 times a day. The dose should be tailored to the needs of the patient and may be increased or decreased depending on the severity of the symptoms. Dosage adjustments may be made after initiation of drug therapy or during exacerbations of the disease. Total daily dosage should not exceed 3,200 mg.

4. CONTRAINDICATIONS

- Known hypersensitivity to fenoprofen or any components of the drug product (4)
- History of asthma, urticaria, or other allergic-type reactions after taking aspirin or other NSAIDs (4)
- In the setting of CABG surgery (4)

5. WARNINGS AND PRECAUTIONS

- Hepatotoxicity: Inform patients of warning signs and symptoms of hepatotoxicity. Discontinue if abnormal liver tests persist or worsen or if clinical signs and symptoms of liver disease develop (5.3)
- Hypertension: Patients taking some antihypertensive medications may have impaired response to these therapies when taking NSAIDs. Monitor blood pressure (5.4, 7)
- Heart Failure and Edema: Avoid use of FENOPROFEN CALCIUM in patients with severe heart failure unless benefits are expected to outweigh risk of worsening heart failure (5.5)
- Renal Toxicity: Monitor renal function in patients with renal or hepatic impairment, heart failure, dehydration, or hypovolemia. Avoid use of FENOPROFEN CALCIUM in patients with advanced renal disease unless benefits are expected to outweigh risk of worsening renal function (5.6)
- Anaphylactic Reactions: Seek emergency help if an anaphylactic reaction occurs (5.7)
- Exacerbation of Asthma Related to Aspirin Sensitivity: FENOPROFEN CALCIUM is contraindicated in patients with aspirin-sensitive asthma. Monitor patients with preexisting asthma (without aspirin sensitivity) (5.8)
- Serious Skin Reactions: Discontinue FENOPROFEN CALCIUM at first appearance of skin rash or other signs of hypersensitivity (5.9)
- Premature Closure of Fetal Ductus Arteriosus: Avoid use in pregnant women starting at 30 weeks gestation (5.10, 8.1)
- Hematologic Toxicity: Monitor hemoglobin or hematocrit in patients with any signs or symptoms of anemia (5.11, 7)

6. ADVERSE REACTIONS

Most common adverse reactions (incidence ≥ 5%) are Dyspepsia, headache, somnolence, nausea, dizziness, constipation, nervousness, asthenia, and peripheral edema.

To report SUSPECTED ADVERSE REACTIONS, FDA at 1-800-FDA-1088 or www.fda.gov/medwatch (6)

7. DRUG INTERACTIONS

- Drugs that Interfere with Hemostasis (e.g. warfarin, aspirin, SSRIs/SNRIs): Monitor patients for bleeding who are concomitantly taking FENOPROFEN CALCIUM with drugs that interfere with hemostasis. Concomitant use of FENOPROFEN CALCIUM and analgesic doses of aspirin is not generally recommended (7)
- ACE Inhibitors, Angiotensin Receptor Blockers (ARB), or Beta-Blockers: Concomitant use with FENOPROFEN CALCIUM may diminish the antihypertensive effect of these drugs. Monitor blood pressure (7)
- ACE Inhibitors and ARBs: Concomitant use with FENOPROFEN CALCIUM in elderly, volume depleted, or those with renal impairment may result in deterioration of renal function. In such high risk patients, monitor for signs of worsening renal function (7)
- Diuretics: NSAIDs can reduce natriuretic effect of furosemide and thiazide diuretics. Monitor patients to assure diuretic efficacy including antihypertensive effects (7)
- Digoxin: Concomitant use with FENOPROFEN CALCIUM can increase serum concentration and prolong half-life of digoxin. Monitor serum digoxin levels (7)

8. USE IN SPECIFIC POPULATIONS

Pregnancy: Use of NSAIDs during the third trimester of pregnancy increases the risk of premature closure of the fetal ductus arteriosus. Avoid use of NSAIDs in pregnant women starting at 30 weeks gestation (5.10, 8.1)

Infertility: NSAIDs are associated with reversible infertility. Consider withdrawal of FENOPROFEN CALCIUM in women who have difficulties conceiving (8.3)

FULL PRESCRIBING INFORMATION

WARNING: RISK OF SERIOUS CARDIOVASCULAR AND GASTROINTESTINAL EVENTS

Cardiovascular Thrombic Events

Non-Steroidal Anti-Inflammatory drugs (NSAIDs) cause an increased risk of serious cardiovascular thrombotic events, including myocardial infarction and stroke, which can be fatal. This risk may occur early in treatment and may increase with duration of use. [ see Warnings and Precautions (5.1) ].

FENOPROFEN CALCIUM ® is contraindicated in the setting of coronary artery bypass graft (CABG) surgery [ see Contraindications (4) and Warnings and precautions (5.1) ].

Gastrointestinal Bleeding, Ulceration, and Perforation

NSAIDs cause an increased risk of serious gastrointestinal (GI) adverse events including bleeding, ulceration, and perforation of stomach or intestines, which can be fatal. These events can occur at any time during use and without warning symptoms. Elderly patients and patients with a prior history of peptic ulcer disease and/or GI bleeding are at greater risk for serious GI events [ see Warnings and Precautions (5.2) ].

1. INDICATIONS AND USAGE

FENOPROFEN CALCIUM is indicated for:

Relief of mild to moderate pain in adults.

Relief of the signs and symptoms of rheumatoid arthrites.

Relief of the signs and symptoms of osteoarthritis.

2. DOSAGE AND ADMINISTRATION

2.1 General Dosing

Carefully consider the potential benefits and risks of FENOPROFEN CALCIUM and other treatment options before deciding to use FENOPROFEN CALCIUM. Use lowest effective dosage for the shortest duration consistent with individual patient treatment goals [ see Warnings and Precautions (5) ].
Fenoprofen Calcium may be administered with meals or with milk. Although the total amount absorbed is not affected, peak blood levels are delayed and diminished.
Patients with rheumatoid arthritis generally seem to require larger doses of Fenoprofen calcium than do those with osteoarthritis. The smallest dose that yields acceptable control should be employed.
Although improvement may be seen in a few days in many patients, an additional 2 to 3 weeks may be required to gauge the full benefits of therapy.

2.2 Analgesia

For the treatment of mild to moderate pain, the recommended dosage is 200 mg given orally every 4 to 6 hours, as needed.

2.3 Rheumatoid Arthritis and Osteoarthritis

For the relief of signs and symptoms of rheumatoid arthritis or osteoarthritis the recommended dose is 400 to 600 mg given orally, 3 or 4 times a day. The dose should be tailored to the needs of the patient and may be increased or decreased depending on the severity of the symptoms. Dosage adjustments may be made after initiation of drug therapy or during exacerbations of the disease. Total daily dosage should not exceed 3,200 mg.

4. CONTRAINDICATIONS

FENOPROFEN CALCIUM is contraindicated in the following patients:

- Known hypersensitivity (e.g., anaphylactic reactions and serious skin reactions) to fenoprofen or any components of the drug product [ see Warnings and Precautions (5.7, 5.9) ]
- History of asthma, urticaria, or other allergic-type reactions after taking aspirin or other NSAIDs. Severe, sometimes fatal, anaphylactic reactions to NSAIDs have been reported in such patients [ see Warnings and Precautions (5.7, 5.8) ]
- In the setting of coronary artery bypass graft (CABG) surgery [ see Warnings and Precautions (5.1) ]

5. WARNINGS AND PRECAUTIONS

5.1 Cardiovascular Thrombotic Events

Clinical trials of several COX-2 selective and nonselective NSAIDs of up to three years duration have shown an increased risk of serious cardiovascular (CV) thrombotic events, including myocardial infarction (MI) and stroke, which can be fatal. Based on available data, it is unclear that the risk for CV thrombotic events is similar for all NSAIDs. The relative increase in serious CV thrombotic events over baseline conferred by NSAID use appears to be similar in those with and without known CV disease or risk factors for CV disease. However, patients with known CV disease or risk factors had a higher absolute incidence of excess serious CV thrombotic events, due to their increased baseline rate. Some observational studies found that this increased risk of serious CV thrombotic events began as early as the first weeks of treatment. The increase in CV thrombotic risk has been observed most consistently at higher doses.

To minimize the potential risk for an adverse CV event in NSAID-treated patients, use the lowest effective dose for the shortest duration possible. Physicians and patients should remain alert for the development of such events, throughout the entire treatment course, even in the absence of previous CV symptoms. Patients should be informed about the symptoms of serious CV events and the steps to take if they occur.

There is no consistent evidence that concurrent use of aspirin mitigates the increased risk of serious CV thrombotic events associated with NSAID use. The concurrent use of aspirin and an NSAID, such as fenoprofen, increases the risk of serious gastrointestinal (GI) events [ see Warnings and Precautions (5.2) ].

Status Post Coronary Artery Bypass Graft (CABG) Surgery
Two large, controlled clinical trials of a COX-2 selective NSAID for the treatment of pain in the first 10–14 days following CABG surgery found an increased incidence of myocardial infarction and stroke. NSAIDs are contraindicated in the setting of CABG [ see Contraindications (4) ].

Post-MI Patients
Observational studies conducted in the Danish National Registry have demonstrated that patients treated with NSAIDs in the post-MI period were at increased risk of reinfarction, CV-related death, and all-cause mortality beginning in the first week of treatment. In this same cohort, the incidence of death in the first year post-MI was 20 per 100 person years in NSAID-treated patients compared to 12 per 100 person years in non-NSAID exposed patients. Although the absolute rate of death declined somewhat after the first year post-MI, the increased relative risk of death in NSAID users persisted over at least the next four years of follow-up.

Avoid the use of FENOPROFEN CALCIUM in patients with a recent MI unless the benefits are expected to outweigh the risk of recurrent CV thrombotic events. If FENOPROFEN CALCIUM is used in patients with a recent MI, monitor patients for signs of cardiac ischemia.

5.2 Gastrointestinal Bleeding, Ulceration, and Perforation

NSAIDs, including FENOPROFEN CALCIUM, cause serious gastrointestinal (GI) adverse events including inflammation, bleeding, ulceration, and perforation of the esophagus, stomach, small intestine, or large intestine, which can be fatal. These serious adverse events can occur at any time, with or without warning symptoms, in patients treated with NSAIDS. Only one in five patients who develop a serious upper GI adverse event on NSAID therapy is symptomatic. Upper GI ulcers, gross bleeding, or perforation caused by NSAIDs occurred in approximately 1% of patients treated for 3-6 months, and in about 2%-4% of patients treated for one year. However, even short-term NSAID therapy is not without risk.

Risk Factors for GI Bleeding, Ulceration, and Perforation
Patients with a prior history of peptic ulcer disease and/or GI bleeding who used NSAIDs had a greater than 10-fold increased risk of developing a GI bleed compared to patients without these risk factors. Other factors that increase the risk for GI bleeding in patients treated with NSAIDs include longer duration of NSAID therapy; concomitant use of oral corticosteroids, aspirin, anticoagulants, or selective serotonin reuptake inhibitors (SSRIs); smoking; use of alcohol; older age; and poor general health status. Most postmarketing reports of fatal GI events occurred in elderly or debilitated patients. Additionally, patients with advanced liver disease and/or coagulopathy are at increased risk for GI bleeding.

Strategies to Minimize the GI Risks in NSAID-treated Patients:

- Use the lowest effective dosage for the shortest possible duration.
- Avoid administration of more than one NSAID at a time.
- Avoid use in patients at higher risk unless benefits are expected to outweigh theincreased risk of bleeding. For such patients, as well as those with active GIbleeding, consider alternate therapies other than NSAIDs.
- Remain alert for signs and symptoms of GI ulceration and bleeding during NSAID therapy.
- If a serious GI adverse event is suspected, promptly initiate evaluation and treatment, and discontinue FENOPROFEN CALCIUM until a serious GI adverse event is ruled out.
- In the setting of concomitant use of low-dose aspirin for cardiac prophylaxis, monitor patients more closely for evidence of GI bleeding [ see Drug Interactions (7) ].

5.3 Hepatotoxicity

Elevations of ALT or AST (three or more times the upper limit of normal [ULN]) have been reported in approximately 1% of NSAID-treated patients in clinical trials. In addition, rare, sometimes fatal, cases of severe hepatic injury, including fulminant hepatitis, liver necrosis, and hepatic failure have been reported.

Elevations of ALT or AST (less than three times ULN) may occur in up to 15% of patients treated with NSAIDs including fenoprofen.

Inform patients of the warning signs and symptoms of hepatotoxicity (e.g., nausea, fatigue, lethargy, diarrhea, pruritus, jaundice, right upper quadrant tenderness, and "flu-like" symptoms). If clinical signs and symptoms consistent with liver disease develop, or if systemic manifestations occur (e.g., eosinophilia, rash, etc.), discontinue FENOPROFEN CALCIUM immediately, and perform a clinical evaluation of the patient.

5.4 Hypertension

NSAIDs, including FENOPROFEN CALCIUM, can lead to new onset of hypertension or worsening of pre-existing hypertension, either of which may contribute to the increased incidence of CV events. Patients taking angiotensin converting enzyme (ACE) inhibitors, thiazide diuretics, or loop diuretics may have impaired response to these therapies when taking NSAIDs [ see Drug Interactions (7) ].

Monitor blood pressure (BP) during the initiation of NSAID treatment and throughout the course of therapy.

5.5 Heart Failure and Edema

The Coxib and traditional NSAID Trialists’ Collaboration meta-analysis of randomized controlled trials demonstrated an approximately two-fold increase in hospitalizations for heart failure in COX-2 selective-treated patients and nonselective NSAID-treated patients compared to placebo-treated patients. In a Danish National Registry study of patients with heart failure, NSAID use increased the risk of MI, hospitalization for heart failure, and death.

Additionally, fluid retention and edema have been observed in some patients treated with NSAIDs. Use of fenoprofen may blunt the CV effects of several therapeutic agents used to treat these medical conditions (e.g., diuretics, ACE inhibitors, or angiotensin receptor blockers [ARBs]) [ see Drug Interactions (7) ].

Avoid the use of FENOPROFEN CALCIUM in patients with severe heart failure unless the benefits are expected to outweigh the risk of worsening heart failure. If FENOPROFEN CALCIUM is used in patients with severe heart failure, monitor patients for signs of worsening heart failure.

5.6 Renal Toxicity and Hyperkalemia

Renal Toxicity
Long-term administration of NSAIDs has resulted in renal papillary necrosis and other renal injury.

Renal toxicity has also been seen in patients in whom renal prostaglandins have a compensatory role in the maintenance of renal perfusion. In these patients, administration of an NSAID may cause a dose-dependent reduction in prostaglandin formation and, secondarily, in renal blood flow, which may precipitate overt renal decompensation. Patients at greatest risk of this reaction are those with impaired renal function, dehydration, hypovolemia, heart failure, liver dysfunction, those taking diuretics and ACE inhibitors or ARBs, and the elderly. Discontinuation of NSAID therapy is usually followed by recovery to the pretreatment state.

No information is available from controlled clinical studies regarding the use of FENOPROFEN CALCIUM in patients with advanced renal disease. The renal effects of FENOPROFEN CALCIUM may hasten the progression of renal dysfunction in patients with pre-existing renal disease.

Correct volume status in dehydrated or hypovolemic patients prior to initiating FENOPROFEN CALCIUM. Monitor renal function in patients with renal or hepatic impairment, heart failure, dehydration, or hypovolemia during use of FENOPROFEN CALCIUM [ see Drug Interactions (7) ]. Avoid the use of FENOPROFEN CALCIUM in patients with advanced renal disease unless the benefits are expected to outweigh the risk of worsening renal function. If FENOPROFEN CALCIUM is used in patients with advanced renal disease, monitor patients for signs of worsening renal function.

Hyperkalemia
Increases in serum potassium concentration, including hyperkalemia, have been reported with use of NSAIDs, even in some patients without renal impairment. In patients with normal renal function, these effects have been attributed to a hyporeninemic-hypoaldosteronism state.

5.7 Anaphylactic Reactions

Fenoprofen has been associated with anaphylactic reactions in patients with and without known hypersensitivity to fenoprofen and in patients with aspirin-sensitive asthma [ see Contraindications (4) and Warnings and Precautions (5.8) ].

Seek emergency help if an anaphylactic reaction occurs.

5.8 Exacerbation of Asthma Related to Aspirin Sensitivity

A subpopulation of patients with asthma may have aspirin-sensitive asthma which may include chronic rhinosinusitis complicated by nasal polyps; severe, potentially fatal bronchospasm; and/or intolerance to aspirin and other NSAIDs. Because cross-reactivity between aspirin and other NSAIDs has been reported in such aspirin-sensitive patients, FENOPROFEN CALCIUM is contraindicated in patients with this form of aspirin sensitivity [ see Contraindications (4) ]. When FENOPROFEN CALCIUM is used in patients with preexisting asthma (without known aspirin sensitivity), monitor patients for changes in the signs and symptoms of asthma.

5.9 Serious Skin Reactions

NSAIDs, including fenopropfen, can cause serious skin adverse reactions such as exfoliative dermatitis, Stevens-Johnson Syndrome (SJS), and toxic epidermal necrolysis (TEN), which can be fatal. These serious events may occur without warning. Inform patients about the signs and symptoms of serious skin reactions, and to discontinue the use of FENOPROFEN CALCIUM at the first appearance of skin rash or any other sign of hypersensitivity.

FENOPROFEN CALCIUM is contraindicated in patients with previous serious skin reactions to NSAIDs [ see Contraindications (4) ].

5.10 Premature Closure of Fetal Ductus Arteriosus

Fenoprofen may cause premature closure of the fetal ductus arteriosus. Avoid use of NSAIDs, including FENOPROFEN CALCIUM, in pregnant women starting at 30 weeks of gestation (third trimester) [ see Use in Specific Populations (8.1) ].

5.11 Hematologic Toxicity

Anemia has occurred in NSAID-treated patients. This may be due to occult or gross blood loss, fluid retention, or an incompletely described effect on erythropoiesis. If a patient treated with FENOPROFEN CALCIUM has any signs or symptoms of anemia, monitor hemoglobin or hematocrit.

NSAIDs, including FENOPROFEN CALCIUM, may increase the risk of bleeding events. Co-morbid conditions such as coagulation disorders, concomitant use of warfarin, other anticoagulants, antiplatelet agents (e.g., aspirin), serotonin reuptake inhibitors (SSRIs) and serotonin norepinephrine reuptake inhibitors (SNRIs) may increase this risk. Monitor these patients for signs of bleeding [ see Drug Interactions (7) ].

5.12 Masking of Inflammation and Fever

The pharmacological activity of FENOPROFEN CALCIUM in reducing inflammation, and possibly fever, may diminish the utility of diagnostic signs in detecting infections.

5.13 Laboratory Monitoring

Because serious GI bleeding, hepatotoxicity, and renal injury can occur without warning symptoms or signs, consider monitoring patients on long-term NSAID treatment with a CBC and a chemistry profile periodically [ see Warnings and Precautions (5.2, 5.3, 5.6) ].

5.14 Ocular Effects

Studies to date have not shown changes in the eyes attributable to the administration of FENOPROFEN CALCIUM. However, adverse ocular effects have been observed with other anti-inflammatory drugs. Eye examinations, therefore, should be performed if visual disturbances occur in patients taking FENOPROFEN CALCIUM.

5.15 Central Nervous System Effects

Caution should be exercised by patients whose activities require alertness if they experience CNS side effects while taking FENOPROFEN CALCIUM.

5.16 Impact on Hearing

Since the safety of FENOPROFEN CALCIUM has not been established in patients with impaired hearing, these patients should have periodic tests of auditory function during prolonged therapy with FENOPROFEN CALCIUM.

6. ADVERSE REACTIONS

The following adverse reactions are discussed in greater detail in other sections of the labeling:

- Cardiovascular Thrombotic Events [ see Warnings and Precautions (5.1) ]
- GI Bleeding, Ulceration and Perforation [ see Warnings and Precautions (5.2) ]
- Hepatotoxicity [ see Warnings and Precautions (5.3) ]
- Hypertension [ see Warnings and Precautions (5.4) ]
- Heart Failure and Edema [ see Warnings and Precautions (5.5) ]
- Renal Toxicity and Hyperkalemia [ see Warnings and Precautions (5.6) ]
- Anaphylactic Reactions [ see Warnings and Precautions (5.7) ]
- Serious Skin Reactions [ see Warnings and Precautions (5.9) ]
- Hematologic Toxicity [ see Warnings and Precautions (5.11) ]

6.1 Clinical Trials Experience

Because clinical trials are conducted under widely varying conditions, adverse reaction rates observed in the clinical trials of a drug cannot be directly compared to rates in the clinical trials of another drug and may not reflect the rates observed in practice.

During clinical studies for rheumatoid arthritis, osteoarthritis, or mild to moderate pain and studies of pharmacokinetics, complaints were compiled from a checklist of potential adverse reactions, and the following data emerged. These encompass observations in 6,786 patients, including 188 observed for at least 52 weeks. For comparison, data are also presented from complaints received from the 266 patients who received placebo in these same trials. During short-term studies for analgesia, the incidence of adverse reactions was markedly lower than that seen in longer-term studies.

Adverse Drug Reactions Reported in >1% of Patients During Clinical Trials

Digestive System — During clinical trials with Fenoprofen Calcium, the most common adverse reactions were gastrointestinal in nature and occurred in 20.8% of patients receiving Fenoprofen Calcium as compared to 16.9% of patients receiving placebo. In descending order of frequency, these reactions included dyspepsia (10.3% Fenoprofen Calcium vs. 2.3% placebo), nausea (7.7% vs. 7.1%), constipation (7% vs. 1.5%), vomiting (2.6% vs. 1.9%), abdominal pain (2% vs. 1.1%), and diarrhea (1.8% vs. 4.1%). The drug was discontinued because of adverse gastrointestinal reactions in less than 2% of patients during premarketing studies.

Nervous System — The most frequent adverse neurologic reactions were headache (8.7% vs. 7.5%) and somnolence (8.5% vs. 6.4%). Dizziness (6.5% vs. 5.6%), tremor (2.2% vs. 0.4%), and confusion (1.4% vs. none) were noted less frequently. Fenoprofen Calcium was discontinued in less than 0.5% of patients because of these side effects during premarketing studies.

Skin and Appendages— Increased sweating (4.6% vs. 0.4%), pruritus (4.2% vs. 0.8%), and rash (3.7% vs. 0.4%) were reported. Fenoprofen Calcium was discontinued in about 1% of patients because of an adverse effect related to the skin during premarketing studies.

Special Senses — Tinnitus (4.5% vs. 0.4%), blurred vision (2.2% vs. none), and decreased hearing (1.6% vs. none) were reported. Fenoprofen Calcium was discontinued in less than 0.5% of patients because of adverse effects related to the special senses during premarketing studies.

Cardiovascular — Palpitations (2.5% vs. 0.4%). Fenoprofen Calcium was discontinued in about 0.5% of patients because of adverse cardiovascular reactions during premarketing studies.

Miscellaneous — Nervousness (5.7% vs. 1.5%), asthenia (5.4% vs. 0.4%), peripheral edema (5.0% vs. 0.4%), dyspnea (2.8% vs. none), fatigue (1.7% vs. 1.5%), upper respiratory infection (1.5% vs. 5.6%), and nasopharyngitis (1.2% vs. none).

Adverse Drug Reactions Reported in <1% of Patients During Clinical Trials

Digestive System—Gastritis, peptic ulcer with/without perforation, gastrointestinal hemorrhage, anorexia, flatulence, dry mouth, and blood in the stool. Increases in alkaline phosphatase, LDH, SGOT, jaundice, and cholestatic hepatitis, aphthous ulcerations of the buccal mucosa, metallic taste, and pancreatitis.

Cardiovascular—Atrial fibrillation, pulmonary edema, electrocardiographic changes, and supraventricular tachycardia.

Genitourinary Tract—Renal failure, dysuria, cystitis, hematuria, oliguria, azotemia, anuria, interstitial nephritis, nephrosis, and papillary necrosis.

Hypersensitivity—Angioedema (angioneurotic edema).

Hematologic—Purpura, bruising, hemorrhage, thrombocytopenia, hemolytic anemia, aplastic anemia, agranulocytosis, and pancytopenia.

Nervous System—Depression, disorientation, seizures, and trigeminal neuralgia.

Special Senses—Burning tongue, diplopia, and optic neuritis.

Skin and Appendages—Exfoliative dermatitis, toxic epidermal necrolysis, Stevens-Johnson syndrome, and alopecia.

Miscellaneous—Anaphylaxis, urticaria, malaise, insomnia, tachycardia, personality change, lymphadenopathy, mastodynia, and fever.

7. DRUG INTERACTIONS

See Table 1 for clinically significant drug interactions with fenoprophen.

Table 1: Clinically Significant Drug Interactions with Fenoprofen
Drugs That Interfere with Hemostasis
Clinical Impact: | - Fenoprofen and anticoagulants such as warfarin have a synergistic effect on bleeding. The concomitant use of fenoprofen and anticoagulants have an increased risk of serious bleeding compared to the use of either drug alone. - Serotonin release by platelets plays an important role in hemostasis. Case-control and cohort epidemiological studies showed that concomitant use of drugs that interfere with serotonin reuptake and an NSAID may potentiate the risk of bleeding more than an NSAID alone.
Intervention: | Monitor patients with concomitant use of FENOPROFEN CALCIUM with anticoagulants (e.g., warfarin), antiplatelet agents (e.g., aspirin), selective serotonin reuptake inhibitors (SSRIs), and serotonin norepinephrine reuptake inhibitors (SNRIs) for signs of bleeding [ see Warnings and Precautions (5.11) ].
Aspirin
Clinical Impact: | Controlled clinical studies showed that the concomitant use of NSAIDs and analgesic doses of aspirin does not produce any greater therapeutic effect than the use of NSAIDs alone. In a clinical study, the concomitant use of an NSAID and aspirin was associated with a significantly increased incidence of GI adverse reactions as compared to use of the NSAID alone [ see Warnings and Precautions (5.2) ].
Intervention: | Concomitant use of FENOPROFEN CALCIUM and analgesic doses of aspirin is not generally recommended because of the increased risk of bleeding [ see Warnings and Precautions (5.11) ].; FENOPROFEN CALCIUM is not a substitute for low dose aspirin for cardiovascular protection.
ACE Inhibitors, Angiotensin Receptor Blockers, and Beta-Blockers
Clinical Impact: | - NSAIDs may diminish the antihypertensive effect of angiotensin converting enzyme (ACE) inhibitors, angiotensin receptor blockers (ARBs), or beta-blockers (including propranolol). - In patients who are elderly, volume-depleted (including those on diuretic therapy), or have renal impairment, co-administration of an NSAID with ACE inhibitors or ARBs may result in deterioration of renal function, including possible acute renal failure. These effects are usually reversible.
Intervention: | - During concomitant use of FENOPROFEN CALCIUM and ACE-inhibitors, ARBs, or betablockers, monitor blood pressure to ensure that the desired blood pressure is obtained. - During concomitant use of FENOPROFEN CALCIUM ACE-inhibitors or ARBs in patients who are elderly, volume-depleted, or have impaired renal function, monitor for signs of worsening renal function [ see Warnings and Precautions (5.6) ]. - When these drugs are administered concomitantly, patients should be adequately hydrated. Assess renal function at the beginning of the concomitant treatment and periodically thereafter.
Diuretics
Clinical Impact: | Clinical studies, as well as post-marketing observations, showed that NSAIDs reduced the natriuretic effect of loop diuretics (e.g., furosemide) and thiazide diuretics in some patients. This effect has been attributed to the NSAID inhibition of renal prostaglandin synthesis.
Intervention: | During concomitant use of FENOPROFEN CALCIUM with diuretics, observe patients for signs of worsening renal function, in addition to assuring diuretic efficacy including antihypertensive effects [ see Warnings and Precautions (5.6) ].
Digoxin
Clinical Impact: | The concomitant use of fenoprofen with digoxin has been reported to increase the serum concentration and prolong the half-life of digoxin.
Intervention: | During concomitant use of FENOPROFEN CALCIUM and digoxin, monitor serum digoxin levels.
Lithium
Clinical Impact: | NSAIDs have produced elevations in plasma lithium levels and reductions in renal lithium clearance. The mean minimum lithium concentration increased 15%, and the renal clearance decreased by approximately 20%. This effect has been attributed to NSAID inhibition of renal prostaglandin synthesis.
Intervention: | During concomitant use of FENOPROFEN CALCIUM and lithium, monitor patients for signs of lithium toxicity.
Methotrexate
Clinical Impact: | Concomitant use of NSAIDs and methotrexate may increase the risk for methotrexate toxicity (e.g., neutropenia, thrombocytopenia, renal dysfunction).
Intervention: | During concomitant use of FENOPROFEN CALCIUM and methotrexate, monitor patients for methotrexate toxicity.
Cyclosporine
Clinical Impact: | Concomitant use of FENOPROFEN CALCIUM and cyclosporine may increase cyclosporine’s nephrotoxicity.
Intervention: | During concomitant use of FENOPROFEN CALCIUM and cyclosporine, monitor patients for signs of worsening renal function.
NSAIDs and Salicylates
Clinical Impact: | Concomitant use of fenoprofen with other NSAIDs or salicylates (e.g., diflunisal, salsalate) increases the risk of GI toxicity, with little or no increase in efficacy [ see Warnings and Precautions (5.2) ].
Intervention: | The concomitant use of fenoprofen with other NSAIDs or salicylates is not recommended.
Pemetrexed
Clinical Impact: | Concomitant use of FENOPROFEN CALCIUM and pemetrexed may increase the risk of pemetrexed-associated myelosuppression, renal, and GI toxicity (see the pemetrexed prescribing information).
Intervention: | During concomitant use of FENOPROFEN CALCIUM and pemetrexed, in patients with renal impairment whose creatinine clearance ranges from 45 to 79 mL/min, monitor for myelosuppression, renal and GI toxicity.; NSAIDs with short elimination half-lives (e.g., diclofenac, indomethacin) should be avoided for a period of two days before, the day of, and two days following administration of pemetrexed.; In the absence of data regarding potential interaction between pemetrexed and NSAIDs with longer half-lives (e.g., meloxicam, nabumetone), patients taking these NSAIDs should interrupt dosing for at least five days before, the day of, and two days following pemetrexed administration.
Phenobarbital
Clinical Impact: | Chronic administration of phenobarbital, a known enzyme inducer, may be associated with a decrease in the plasma half-life of fenoprofen.
Intervention: | When phenobarbital is added to or withdrawn from treatment, dosage adjustment of FENOPROFEN CALCIUM may be required.
Hydantoins, sulfonamides, or sulfonylureas
Clinical Impact: | In vitro studies have shown that fenoprofen, because of its affinity for albumin, may displace from their binding sites other drugs that are also albumin bound, and this may lead to drug interactions. Theoretically, fenoprofen could likewise be displaced.
Intervention: | Patients receiving hydantoins, sulfonamides, or sulfonylureas should be observed for increased activity of these drugs and, therefore, signs of toxicity from these drugs.

Drug/Laboratory Test Interactions

Amerlex-M kit assay values of total and free triiodothyronine in patients receiving Fenoprofen Calcium have been reported as falsely elevated on the basis of a chemical cross-reaction that directly interferes with the assay. Thyroid-stimulating hormone, total thyroxine, and thyrotropin-releasing hormone response are not affected. Thus, results of the Amerlex-M kit assay should be interpreted with caution in these patients.

8. USE IN SPECIFIC POPULATIONS

8.1 Pregnancy

Risk Summary
Use of NSAIDs, including FENOPROFEN CALCIUM, during the third trimester of pregnancy increases the risk of premature closure of the fetal ductus arteriosus. Avoid use of NSAIDs, including FENOPROFEN CALCIUM, in pregnant women starting at 30 weeks of gestation (third trimester).

There are no adequate and well-controlled studies of FENOPROFEN CALCIUM in pregnant women. Data from observational studies regarding potential embryofetal risks of NSAID use in women in the first or second trimesters of pregnancy are inconclusive. In the general U.S. population, all clinically recognized pregnancies, regardless of drug exposure, have a background rate of 2-4% for major malformations, and 15-20% for pregnancy loss.

In animal reproduction studies, embryo-fetal lethality and skeletal abnormalities were noted in offspring of pregnant rabbits following oral administration of fenoprofen during organogenesis at 0.6 times the maximum human daily dose of 3200 mg/day. However, there were no major malformations noted following oral administration of fenoprofen calcium to pregnant rats and rabbits during organogenesis at exposures up to 0.3 and 0.6 times the maximum human daily dose of 3200 mg/day.

Based on animal data, prostaglandins have been shown to have an important role in endometrial vascular permeability, blastocyst implantation, and decidualization. In animal studies, administration of prostaglandin synthesis inhibitors such as fenoprofen, resulted in increased pre- and post-implantation loss.

Clinical Considerations
Labor or Delivery
There are no studies on the effects of FENOPROFEN CALCIUM during labor or delivery. In animal studies, NSAIDS, including fenoprofen, inhibit prostaglandin synthesis, cause delayed parturition, and increase the incidence of stillbirth.

Data
Human Data
There are no adequate and well-controlled studies of FENOPROFEN CALCIUM in pregnant women. Data from observational studies regarding potential embryofetal risks of NSAID use in women in the first or second trimesters of pregnancy are inconclusive.

Animal data
Pregnant rats were treated with fenoprofen using oral doses of 50 or 100 mg/kg (0.15 times and 0.3 times the maximum human daily dose (MHDD) of 3200 mg/day based on body surface area comparison) during the period of organogenesis. No major malformations were noted and there was no evidence of maternal toxicity at these doses, however, the exposures were below the exposures that will occur in humans.

Pregnant rabbits were treated with fenoprofen using oral doses of 50 or 100 mg/kg (0.3 times and 0.6 times the MHDD of 3200 mg/day based on body surface area comparison) during the period of organogenesis. Maternal toxicity (mortality) was noted in the high dose animals. Although no major malformations were noted, there was an increased incidence of embryo-fetal lethality and skeletal abnormalities were present at 0.6 times the MHDD.

Pregnant rats were treated from Gestation Day 14 through Post-Natal Day 20 with oral doses of fenoprofen of 6.25, 12.5, 25, 50, or 100 mg/kg (0.02, 0.04, 0.08, 0.15, or 0.3 times the MDD of 3200 mg/day based on body surface area comparison). All doses produced significant toxicity, including vaginal bleeding, prolonged parturition, increased stillbirths, and maternal deaths.

Pregnant rats were treated from Gestation Day 6 through Gestation Day 19 and Post Partum Day 1 to 20 (excluding parturition) with an oral dose of fenoprofen of 100 mg/kg (0.3 times the MDD of 3200 mg/day based on body surface area comparison) demonstrated only a small increase in the incidence of impaired parturition despite the presence of maternal toxicity (gastrointestinal ulceration and renal toxicity).

8.2 Lactation

Risk Summary
In a published study, after a dose of 600 mg every 6 hours for 4 days in postpartum mothers, breastmilk fenoprofen levels were reportedly 1.6% of those in maternal plasma. The developmental and health benefits of breastfeeding should be considered along with the mother’s clinical need for FENOPROFEN CALCIUM and any potential adverse effects on the breastfed infant from the FENOPROFEN CALCIUM or from the underlying maternal condition.

8.3 Females and Males of Reproductive Potential

Infertility
Females
Based on the mechanism of action, the use of prostaglandin-mediated NSAIDs, including FENOPROFEN CALCIUM, may delay or prevent rupture of ovarian follicles, which has been associated with reversible infertility in some women. Published animal studies have shown that administration of prostaglandin synthesis inhibitors has the potential to disrupt prostaglandinmediated follicular rupture required for ovulation. Small studies in women treated with NSAIDs have also shown a reversible delay in ovulation. Consider withdrawal of NSAIDs, including FENOPROFEN CALCIUM, in women who have difficulties conceiving or who are undergoing investigation of infertility.

8.4 Pediatric Use

Safety and effectiveness in pediatric patients under the age of 18 have not been established.

8.5 Geriatric Use

Elderly patients, compared to younger patients, are at greater risk for NSAID-associated serious cardiovascular, gastrointestinal, and/or renal adverse reactions. If the anticipated benefit for the elderly patient outweighs these potential risks, start dosing at the low end of the dosing range, and monitor patients for adverse effects [ see Warnings and Precautions (5.1, 5.2, 5.3, 5.6, 5.13) ].

10. OVERDOSAGE

Symptoms following acute NSAID overdosages have been typically limited to lethargy, drowsiness, nausea, vomiting, and epigastric pain, which have been generally reversible with supportive care. Gastrointestinal bleeding has occurred. Hypertension, acute renal failure, respiratory depression, and coma have occurred, but were rare [ see Warnings and Precautions (5.1, 5.2, 5.4, 5.6) ].

Manage patients with symptomatic and supportive care following an NSAID overdosage. There are no specific antidotes. Consider emesis and/or activated charcoal (60 to 100 grams in adults, 1 to 2 grams per kg of body weight in pediatric patients) and/or osmotic cathartic in symptomatic patients seen within four hours of ingestion or in patients with a large overdosage (5 to 10 times the recommended dosage). Forced diuresis, alkalinization of urine, hemodialysis, or hemoperfusion may not be useful due to high protein binding.

For additional information about overdosage treatment contact a poison control center (1-800-222-1222).

11. DESCRIPTION

FENOPROFEN CALCIUM (fenoprofen calcium, USP) capsules is a nonsteroidal, anti-inflammatory drug available in 400 mg capsule form for oral administration.

The 400 mg capsule is opaque green cap and opaque blue body, imprinted with “NALFON 400 mg" on the cap and “EP 123” on the body.

The chemical name is Benzenaecetic acid, α-methyl-3-phenoxy-, calcium salt dihydrate, (±)-. The molecular weight is 558.65. Its molecular formula is C30H26CaO6•2H2O, and it has the following chemical structure.

Fenoprofen Calcium is an arylacetic acid derivative. It is a white crystalline powder. At 25°C, it dissolves to a 15 mg/mL solution in alcohol (95%). It is slightly soluble in water and insoluble in benzene.The pKa of fenoprofen calcium is 4.5 at 25°C.

Fenoprofen calcium capsules contain fenoprofen calcium as the dihydrate in an amount equivalent to 400 mg (1.65 mmol) of fenoprofen.

Inactive ingredients in Fenoprofen Calcium capsules are crospovidone, magnesium stearate, sodium lauryl sulfate, and talc. In addition, the 400 mg capsules contain gelatin, D&C Yellow #10, FD&C Blue #1, FD&C Red #40, FD&C Yellow #6, and titanium dioxide.

12. CLINICAL PHARMACOLOGY

12.1 Mechanism of Action

Fernoprofen has analgesic, anti-inflammatory, and antipyretic properties.

The mechanism of action of FENOPROFEN CALCIUM, like that of other NSAIDs, is not completely understood but involves inhibition of cyclooxygenase (COX-1 and COX-2).

Fenoprofen is a potent inhibitor of prostaglandin synthesis in vitro. Fenoprofen concentrations reached during therapy have produced in vivo effects. Prostaglandins sensitize afferent nerves and potentiate the action of bradykinin in inducing pain in animal models. Prostaglandins are mediators of inflammation. Because fenoprofen is an inhibitor of prostaglandin synthesis, its mode of action may be due to a decrease of prostaglandins in peripheral tissues.

12.3 Pharmacokinetics

Absorption
Under fasting conditions, fenoprofen is rapidly absorbed, and peak plasma levels of 50 mcg/L are achieved within 2 hours after oral administration of 600 mg doses. Good dose proportionality was observed between 200 and 600 mg doses in fasting male volunteers.

Distribution
Fenoprofen is highly bound (99%) to albumin.

Elimination

Metabolism
The plasma half-life is approximately 3 hours.

Excretion
About 90% of a single oral dose is eliminated within 24 hours as fenoprofen glucuronide and 4'-hydroxyfenoprofen glucuronide, the major urinary metabolites of fenoprofen.

Specific Populations

Gertatrics
Peak plasma levels of fenoprofen in normal elderly volunteers were similar to those observed in normal young volunteers. Elderly volunteers had a mean plasma clearance of 2.2 L/hour while plasma clearance of fenoprofen in normal young volunteers ranged from 3 to 3.5 L/hour. The overall elimination rate constant, plasma half-life and ratio of renal to nonrenal clearance of fenoprofen was the same in elderly and young volunteers. The 30 to 60% decrease in plasma clearance is due to a decrease in the volume of distribution in the body.

Drug Interaction Studies
Aspirin: When NSAIDs were administered with aspirin, the protein binding of NSAIDs were reduced, although the clearance of free NSAID was not altered. The clinical significance of this interaction is not known. See Table 1 for clinically significant drug interactions of NSAIDs with aspirin [ see Drug Interactions (7) ].

Antacid: The concomitant administration of antacid (containing both aluminum and magnesium hydroxide) does not interfere with absorption of fenoprofen.

13 NONCLINICAL TOXICOLOGY

Carcinogenesis
Long-term studies in animals to evaluate the carcinogenic potential of fenoprofen have not been conducted.

Mutagenesis
Studies to evaluate the genotoxic potential of fenoprofen have not been conducted.

Impairment of Fertility
Female and Male rats were treated with 60 to 70 mg/kg/day or 120 to 150 mg/kg/day fenoprofen calcium via the diet (approximately 0.2 or 0.4 times the maximum human daily dose of 3200 mg/day based on body surface area comparison, respectively). Male rats were treated from 77 days prior to mating and during mating. Female rats were treated from 14 days prior to mating and through gestation. Pregnancy rates were slightly reduced in the low and high dose groups compared to controls. There was no adverse effect on implantations, resorptions, or live fetuses.

14. CLINICAL STUDIES

FENOPROFEN CALCIUM is a nonsteroidal, anti-inflammatory, antiarthritic drug that also possesses analgesic and antipyretic activities. Its exact mode of action is unknown, but it is thought that prostaglandin synthetase inhibition is involved.

Results in humans demonstrate that fenoprofen has both anti-inflammatory and analgesic actions. The emergence and degree of erythemic response were measured in adult male volunteers exposed to ultraviolet irradiation. The effects of FENOPROFEN CALCIUM, aspirin, and indomethacin were each compared with those of a placebo. All 3 drugs demonstrated antierythemic activity.

In all patients with rheumatoid arthritis, the anti-inflammatory action of FENOPROFEN CALCIUM has been evidenced by relief of pain, increase in grip strength, and reductions in joint swelling, duration of morning stiffness, and disease activity (as assessed by both the investigator and the patient). The anti-inflammatory action of FENOPROFEN CALCIUM has also been evidenced by increased mobility (i.e., a decrease in the number of joints having limited motion).

The use of FENOPROFEN CALCIUM in combination with gold salts or corticosteroids has been studied in patients with rheumatoid arthritis. The studies, however, were inadequate in demonstrating whether further improvement is obtained by adding FENOPROFEN CALCIUM to maintenance therapy with gold salts or steroids. Whether or not FENOPROFEN CALCIUM used in conjunction with partially effective doses of a corticosteroid has a “steroid-sparing” effect is unknown.

In patients with osteoarthritis, the anti-inflammatory and analgesic effects of FENOPROFEN CALCIUM have been demonstrated by reduction in tenderness as a response to pressure and reductions in night pain, stiffness, swelling, and overall disease activity (as assessed by both the patient and the investigator). These effects have also been demonstrated by relief of pain with motion and at rest and increased range of motion in involved joints.

In patients with rheumatoid arthritis and osteoarthritis, clinical studies have shown FENOPROFEN CALCIUM to be comparable to aspirin in controlling the aforementioned measures of disease activity, but mild gastrointestinal reactions (nausea, dyspepsia) and tinnitus occurred less frequently in patients treated with FENOPROFEN CALCIUM than in aspirin-treated patients. It is not known whether FENOPROFEN CALCIUM causes less peptic ulceration than does aspirin.

In patients with pain, the analgesic action of Fenoprofen calcium has produced a reduction in pain intensity, an increase in pain relief, improvement in total analgesia scores, and a sustained analgesic effect.

16. HOW SUPPLIED/STORAGE AND HANDLING

Fenoprofen calcium® (fenoprofen calcium, USP) are available in capsule form for oral administration, and are supplied as following:
● The 400 mg capsule has an opaque green cap and an opaque blue body, imprinted with "NALFON 400 mg" on the cap and "EP 123" on the body. NDC 0276-0503-90 Bottles of 90.

Storage:
Store at room temperature 20°C to 25°C (68°F to 77°F); excursions permitted between 15°C to 30°C (59°F to 86°F) [see USP Controlled Room Temperature].
Preserve in well-closed containers

17. PATIENT COUNSELING INFORMATION

Advise the patient to read the FDA-approved patient labeling (Medication Guide) that accompanies each prescription dispensed. Inform patients, families, or their caregivers of the following information before initiating therapy with FENOPROFEN CALCIUM and periodically during the course of ongoing therapy.

Cardiovascular Thrombotic Events

Advise patients to be alert for the symptoms of cardiovascular thrombotic events, including chest pain, shortness of breath, weakness, or slurring of speech, and to report any of these symptoms to their health care provider immediately [ see Warnings and Precautions (5.1) ].

Gastrointestinal Bleeding, Ulceration, and Perforation
Advise patients to report symptoms of ulcerations and bleeding, including epigastric pain, dyspepsia, melena, and hematemesis to their health care provider. In the setting of concomitant use of low-dose aspirin for cardiac prophylaxis, inform patients of the increased risk for and the signs and symptoms of GI bleeding [ see Warnings and Precautions (5.2) ].

Hepatotoxicity
Inform patients of the warning signs and symptoms of hepatotoxicity (e.g., nausea, fatigue, lethargy, pruritus, diarrhea, jaundice, right upper quadrant tenderness, and “flu-like” symptoms). If these occur, instruct patients to stop FENOPROFEN CALCIUM and seek immediate medical therapy [ see Warnings and Precautions (5.3) ].

Heart Failure and Edema
Advise patients to be alert for the symptoms of congestive heart failure including shortness of breath, unexplained weight gain, or edema and to contact their healthcare provider if such symptoms occur [ see Warnings and Precautions (5.5) ].

Anaphylactic Reactions
Inform patients of the signs of an anaphylactic reaction (e.g., difficulty breathing, swelling of the face or throat). Instruct patients to seek immediate emergency help if these occur [ see Contraindications (4) and Warnings and Precautions (5.7) ].

Serious Skin Reactions
Advise patients to stop FENOPROFEN CALCIUM immediately if they develop any type of rash and to contact their healthcare provider as soon as possible [ see Warnings and Precautions (5.9) ].

Female Fertility
Advise females of reproductive potential who desire pregnancy that NSAIDs, including FENOPROFEN CALCIUM, may be associated with a reversible delay in ovulation [ see Use in Specific Populations (8.3) ]

Fetal Toxicity
Inform pregnant women to avoid use of FENOPROFEN CALCIUM and other NSAIDs starting at 30 weeks gestation because of the risk of the premature closing of the fetal ductus arteriosus [ see Warnings and Precautions (5.10) and Use in Specific Populations (8.1) ].

Avoid Concomitant Use of NSAIDs
Inform patients that the concomitant use of FENOPROFEN CALCIUM with other NSAIDs or salicylates (e.g., diflunisal, salsalate) is not recommended due to the increased risk of gastrointestinal toxicity, and little or no increase in efficacy [ see Warnings and Precautions (5.2) and Drug Interactions (7) ]. Alert patients that NSAIDs may be present in “over the counter” medications for treatment of colds, fever, or insomnia.

Use of NSAIDS and Low-Dose Aspirin
Inform patients not to use low-dose aspirin concomitantly with FENOPROFEN CALCIUM until they talk to their healthcare provider [ see Drug Interactions (7) ].

Medication Guide

What is the most important information I should know about medicines called Nonsteroidal Anti-inflammatory Drugs (NSAIDs)? NSAIDs can cause serious side effects, including:

Increased risk of a heart attack or stroke that can lead to death. This risk may happen early in treatment and may increase:

- with increasing doses of NSAIDs
- with longer use of NSAIDs Do not take NSAIDs right before or after a heart surgery called a “coronary artery bypass graft (CABG).” Avoid taking NSAIDs after a recent heart attack, unless your healthcare provider tells you to. You may have an increased risk of another heart attack if you take NSAIDs after a recent heart attack.

Increased risk of bleeding, ulcers, and tears (perforation) of the esophagus (tube leading from the mouth to the stomach), stomach and intestines:

- anytime during use o without warning symptoms
- that may cause death

The risk of getting an ulcer or bleeding increases with

- past history of stomach ulcers, or stomach or intestinal bleeding with use of NSAIDs
- taking medicines called “corticosteroids”, “anticoagulants”, “SSRIs”, or “SNRIs”
- increasing doses of NSAIDs
- older age
- longer use of NSAIDs
- poor health
- smoking
- advanced liver disease
- drinking alcohol
- bleeding problems

NSAIDs should only be used:

- exactly as prescribed o at the lowest dose possible for your treatment
- for the shortest time needed

What are NSAIDs? NSAIDs are used to treat pain and redness, swelling, and heat (inflammation) from medical conditions such as different types of arthritis, menstrual cramps, and other types of short-term pain.

Who should not take NSAIDs? Do not take NSAIDs:

- if you have had an asthma attack, hives, or other allergic reaction with aspirin or any other NSAIDs.
- right before or after heart bypass surgery.

Before taking NSAIDs, tell your healthcare provider about all of your medical conditions, including if you:

- have liver or kidney problems
- have high blood pressure
- have asthma
- are pregnant or plan to become pregnant. Talk to your healthcare provider if you are considering taking NSAIDs during pregnancy. You should not take NSAIDs after 29 weeks of pregnancy.
- are breastfeeding or plan to breast feed.

Tell your healthcare provider about all of the medicines you take, including prescription or over-the-counter medicines, vitamins or herbal supplements. NSAIDs and some other medicines can interact with each other and cause serious side effects. Do not start taking any new medicine without talking to your healthcare provider first.

What are the possible side effects of NSAIDs? NSAIDs can cause serious side effects, including

- new or worse high blood pressure
- heart failure
- liver problems including liver failure
- kidney problems including kidney failure
- low red blood cells (anemia)
- life-threatening skin reactions
- life-threatening allergic reactions

Other side effects of NSAIDs include: stomach pain, constipation, diarrhea, gas, heartburn, nausea, vomiting, and dizziness.

Get emergency help right away if you get any of the following symptoms

- shortness of breath or trouble breathing
- slurred speech
- chest pain
- swelling of the face or throat
- weakness in one part or side of your body

Stop taking your NSAID and call your healthcare provider right away if you get any of the following symptoms:

- nausea
- vomit blood
- more tired or weaker than usual
- there is blood in your bowel movement or it is
- diarrhea black and sticky like tar
- itching
- unusual weight gain
- your skin or eyes look yellow
- skin rash or blisters with fever
- indigestion or stomach pain
- swelling of the arms, legs, hands and feet
- flu-like symptoms

If you take too much of your NSAID, call your healthcare provider or get medical help right away.

These are not all the possible side effects of NSAIDs. For more information, ask your healthcare provider or pharmacist about NSAIDs. Call your doctor for medical advice about side effects. You may report side effects to FDA at 1-800-FDA-1088.

Other information about NSAIDs:

Aspirin is an NSAID but it does not increase the chance of a heart attack. Aspirin can cause bleeding in the brain, stomach, and intestines. Aspirin can also cause ulcers in the stomach and intestines. Some NSAIDs are sold in lower doses without a prescription (over-the-counter). Talk to your healthcare provider before using over-the-counter NSAIDs for more than 10 days.

General information about the safe and effective use of NSAIDs Medicines are sometimes prescribed for purposes other than those listed in a Medication Guide. Do not use NSAIDs for a condition for which it was not prescribed. Do not give NSAIDs to other people, even if they have the same symptoms that you have. It may harm them. If you would like more information about NSAIDs, talk with your healthcare provider. You can ask your pharmacist or healthcare provider for information about NSAIDs that is written for health professionals.